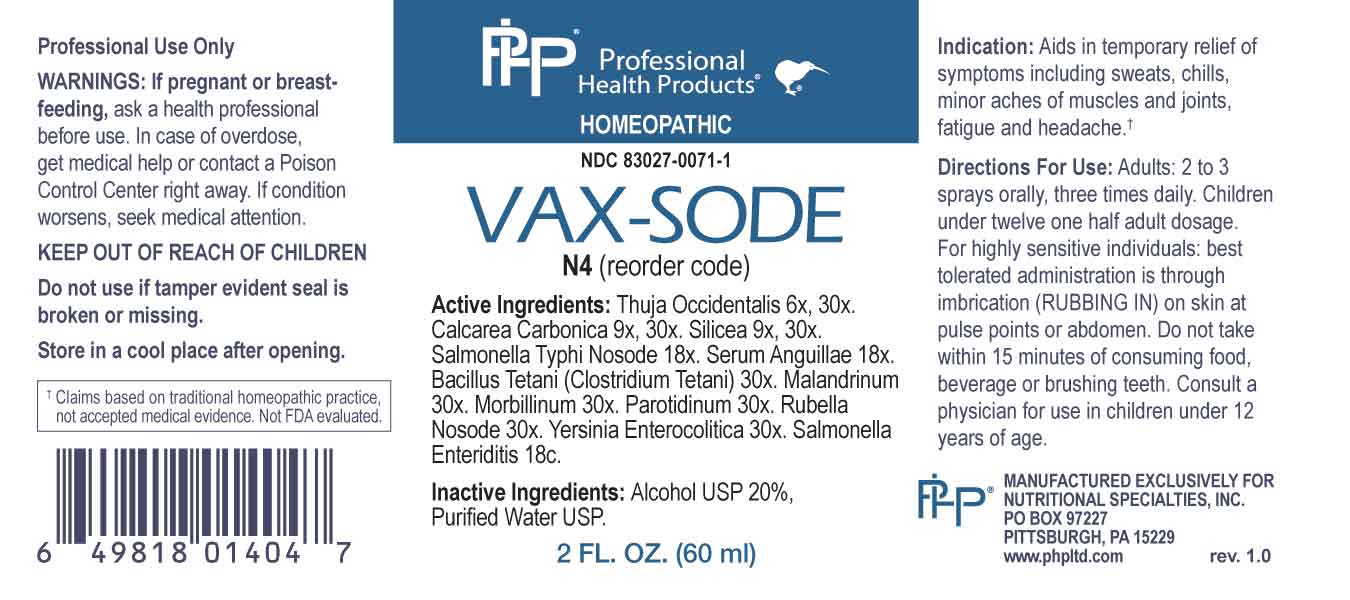 DRUG LABEL: Vax Sode
NDC: 83027-0071 | Form: SPRAY
Manufacturer: Nutritional Specialties, Inc.
Category: homeopathic | Type: HUMAN OTC DRUG LABEL
Date: 20250515

ACTIVE INGREDIENTS: THUJA OCCIDENTALIS LEAFY TWIG 6 [hp_X]/1 mL; OYSTER SHELL CALCIUM CARBONATE, CRUDE 9 [hp_X]/1 mL; SILICON DIOXIDE 9 [hp_X]/1 mL; SALMONELLA ENTERICA ENTERICA SEROVAR TYPHI 18 [hp_X]/1 mL; ANGUILLA ROSTRATA BLOOD SERUM 18 [hp_X]/1 mL; CLOSTRIDIUM TETANI 30 [hp_X]/1 mL; VACCINIA VIRUS 30 [hp_X]/1 mL; MEASLES VIRUS 30 [hp_X]/1 mL; MUMPS VIRUS 30 [hp_X]/1 mL; RUBELLA VIRUS 30 [hp_X]/1 mL; YERSINIA ENTEROCOLITICA 30 [hp_X]/1 mL; SALMONELLA ENTERICA ENTERICA SEROVAR ENTERITIDIS 18 [hp_C]/1 mL
INACTIVE INGREDIENTS: WATER; ALCOHOL

DRUG FACTS:

ACTIVE INGREDIENTS:

Thuja Occidentalis 6X, 30X, Calcarea Carbonica 9X, 30X, Silicea 9X, 30X, Salmonella Typhi Nosode 18X, Serum Anguillae 18X, Bacillus Tetani (Clostridium Tetani) 30X, Malandrinum 30X, Morbillinum 30X, Parotidinum 30X, Rubella Nosode 30X, Yersinia Enterocolitica 30X, Salmonella Enteriditis 18C.

PURPOSE:

Aids in temporary relief of symptoms including sweats, chills, minor aches of muscles and joints, fatigue and headache.†

†Claims based on traditional homeopathic practice, not accepted medical evidence. Not FDA evaluated.

WARNINGS:

Professional Use Only

If pregnant or breast-feeding, ask a health professional before use.

In case of overdose, get medical help or contact a Poison Control Center right away.

If condition worsens, seek medical attention.

KEEP OUT OF REACH OF CHILDREN

Do not use if tamper evident seal is broken or missing.

Store in a cool place after opening

KEEP OUT OF REACH OF CHILDREN:

In case of overdose, get medical help or contact a Poison Control Center right away.

DIRECTIONS:

Adults: 2 to 3 sprays orally, three times daily. Children under twelve one half adult dosage.

For high sensitive individuals: best tolerated administration is through imbrication (RUBBING IN) on skin at pulse points or abdomen.

Do not take within 15 minutes of consuming food, beverage or brushing teeth. Consult a physician for use in children under 12 years of age.

INDICATIONS:

Aids in temporary relief of symptoms including sweats, chills, minor aches of muscles and joints, fatigue and headache.†

†Claims based on traditional homeopathic practice, not accepted medical evidence. Not FDA evaluated.

INACTIVE INGREDIENTS:

Alcohol USP 20%, Purified Water USP.

QUESTIONS:

MANUFACTURED EXCLUSIVELY FOR

NUTRITIONAL SPECIALTIES, INC.

PO BOX 97227

PITTSBURG, PA 15229

www.phpltd.com

PACKAGE LABEL DISPLAY:

Professional

Health Products

HOMEOPATHIC

NDC 83027-0071-1

VAX-SODE

2 FL. OZ (60 ml)